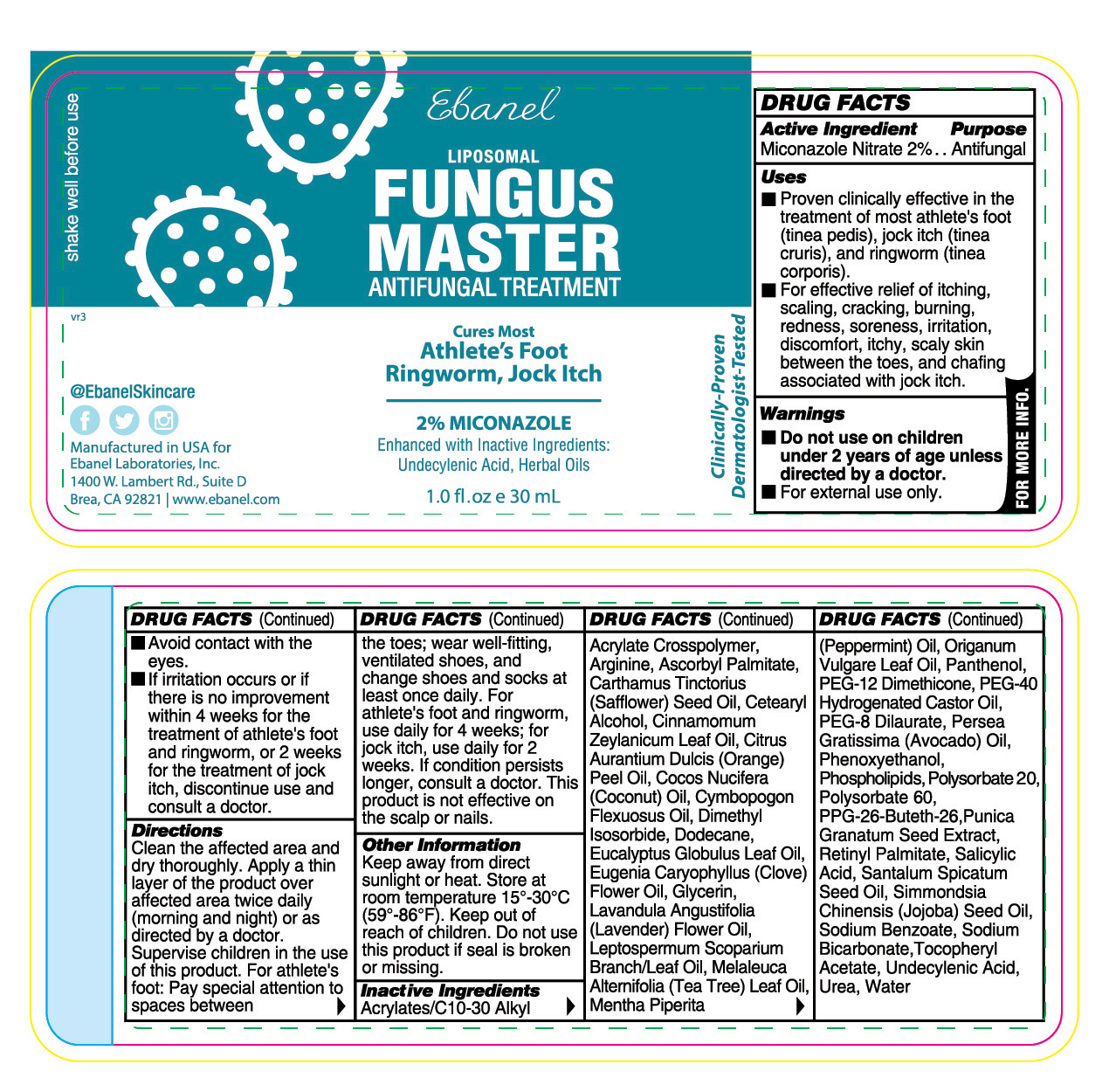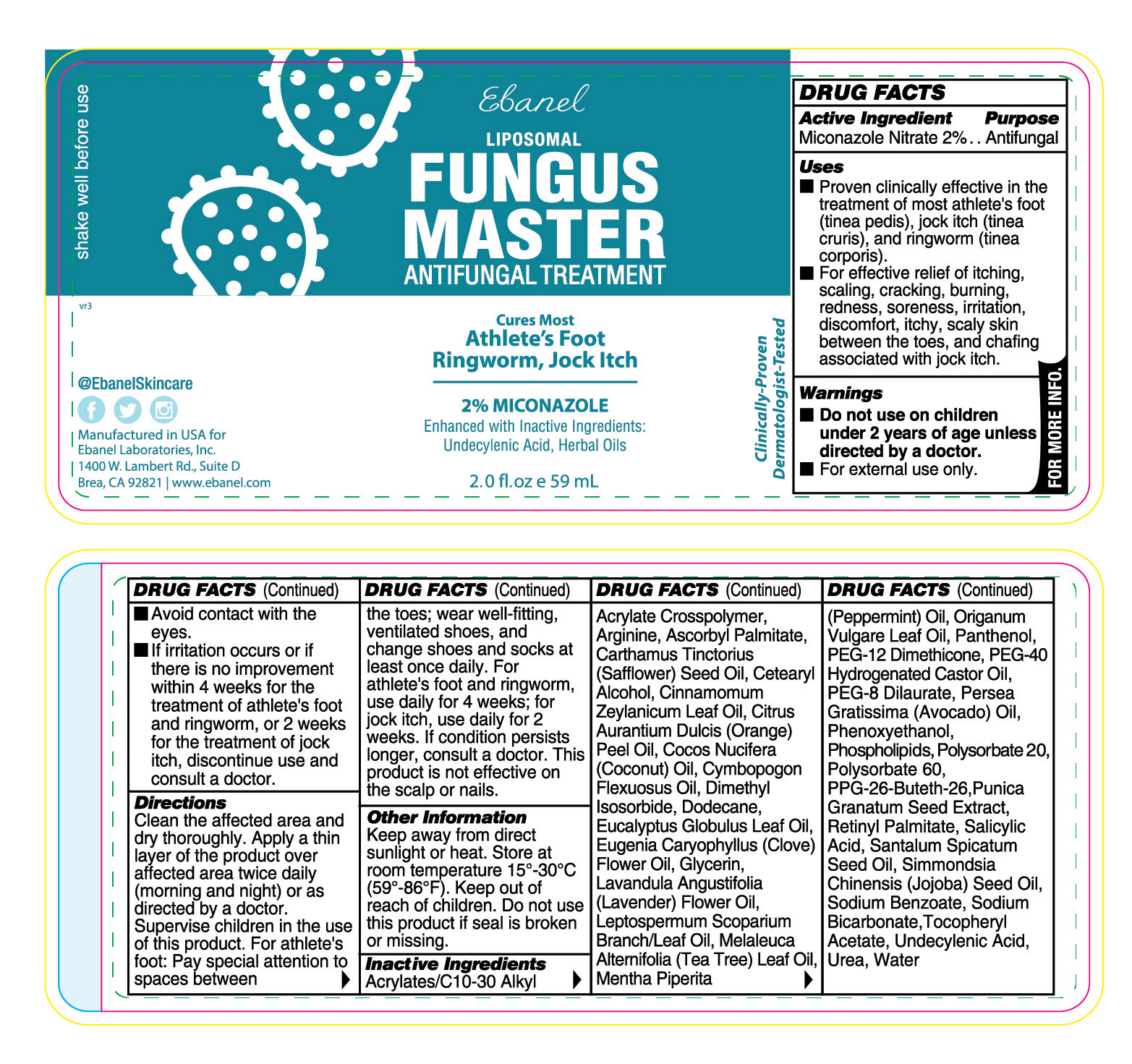 DRUG LABEL: Fungus Master
NDC: 63742-098 | Form: LOTION
Manufacturer: Clinical Resolution Laboratory, Inc.
Category: otc | Type: HUMAN OTC DRUG LABEL
Date: 20250606

ACTIVE INGREDIENTS: MICONAZOLE NITRATE 20 mg/1 g
INACTIVE INGREDIENTS: MENTHA PIPERITA (PEPPERMINT) OIL; PANTHENOL; PEG-12 DIMETHICONE; UREA; PEG-40 HYDROGENATED CASTOR OIL; CAPRYLYL GLYCOL; CITRUS AURANTIUM DULCIS (ORANGE) PEEL OIL; DIMETHYL ISOSORBIDE; POLYSORBATE 60; MELALEUCA ALTERNIFOLIA (TEA TREE) LEAF OIL; TRIETHANOLAMINE; ACRYLATES/C10-30 ALKYL ACRYLATE CROSSPOLYMER (60000 MPA.S); PHENOXYETHANOL; HEXYLENE GLYCOL; LEPTOSPERMUM SCOPARIUM BRANCH/LEAF OIL; BUTYROSPERMUM PARKII (SHEA) BUTTER; CYMBOPOGON FLEXUOSUS OIL; HYDROXYETHYL ACRYLATE/SODIUM ACRYLOYLDIMETHYL TAURATE COPOLYMER (45000 MPA.S AT 1%); UNDECYLENIC ACID; CINNAMOMUM ZEYLANICUM LEAF OIL; SIMMONDSIA CHINENSIS (JOJOBA) SEED OIL; SODIUM BICARBONATE; GLYCERIN; EUGENIA CARYOPHYLLUS (CLOVE) BUD OIL; COCOS NUCIFERA (COCONUT) OIL; ORIGANUM VULGARE LEAF OIL; DISODIUM EDTA-COPPER; POLYSORBATE 20; LAVANDULA ANGUSTIFOLIA (LAVENDER) OIL; FUSANUS SPICATUS WOOD OIL; SODIUM BENZOATE; PPG-26-BUTETH-26; PEG-4 DILAURATE; SALICYLIC ACID; CETEARYL ALCOHOL; ARGININE HYDROCHLORIDE; ETHYLHEXYLGLYCERIN; EUCALYPTUS OIL; XANTHAN GUM; PERSEA GRATISSIMA (AVOCADO) OIL; SQUALANE; RETINYL PALMITATE; ASCORBYL PALMITATE; .ALPHA.-TOCOPHEROL ACETATE, D-; DODECANE; EGG PHOSPHOLIPIDS; WATER

Active Ingredient: Miconazole Nitrate 2%

Directions

Clean the affected area and dry thoroughly. Apply a thin layer of the product over affected area twice daily (morning and night) or as directed by a doctor. Supervise children in the use of this product. For athlete's foot: Pay special attention to spaces between the toes; wear well-fitting, ventilated shoes, and change shoes and socks at least once daily. For athlete's foot and ringworm, use daily for 4 weeks; for jock itch, use daily for 2 weeks. If condition persists longer, consult a doctor. This product is not effective on the scalp or nails.

Warnings

■ Do not use on children under 2 years of age unless directed by a doctor.

■ For external use only.

■ Avoid contact with the eyes.

■ If irritation occurs or if there is no improvement within 4 weeks for the treatment of athlete's foot and ringworm, or 2 weeks for the treatment of jock itch, discontinue use and consult a doctor.

Uses

■ Proven clinically effective in the treatment of most athlete's foot (tinea pedis), jock itch (tinea cruris), and ringworm (tinea corporis).

Other Information

■ Shake well before use.

■ Keep away from direct sunlight or heat. Store at room temperature 15°-30°C (59°-86°F).

■ Keep out of reach of children.

■ In case of accidental overdose or ingestion, call a doctor or poison control center immediately.

■ Do not use this product if seal is broken or missing.

Inactive Ingredients

Acrylates/C10-30 Alkyl Acrylate Crosspolymer, Arginine HCl, Ascorbyl Palmitate, Butyrospermum Parkii (Shea) Butter, Caprylyl Glycol, Cetearyl Alcohol, Cinnamomum Zeylanicum Leaf Oil, Citrus Aurantium Dulcis (Orange) Peel Oil, Cocos Nucifera (Coconut) Oil, Cymbopogon Flexuosus Oil, Dimethyl Isosorbide, Disodium EDTA, Dodecane, Ethylhexylglycerin, Eucalyptus Globulus Leaf Oil, Eugenia Caryophyllus (Clove) Bud Oil, Fusanus Spicatus Wood (Sandalwood) Oil, Glycerin, Hexylene Glycol, Hydroxyethyl Acrylate/Sodium Acryloyldimethyl Taurate Copolymer, Lavandula Angustifolia (Lavender) Oil, Leptospermum Scoparium Branch/Leaf Oil, Melaleuca Alternifolia (Tea Tree) Leaf Oil, Mentha Piperita (Peppermint) Oil, Origanum Vulgare (Oregano) Leaf Oil, Panthenol, PEG-12 Dimethicone, PEG-4 Dilaurate, PEG-40 Hydrogenated Castor Oil, Persea Gratissima (Avocado) Oil, Phenoxyethanol, Phospholipids, Polysorbate 20, Polysorbate 60, PPG-26-Buteth-26, Retinyl Palmitate, Salicylic Acid, Simmondsia Chinensis (Jojoba) Seed Oil, Sodium Benzoate, Sodium Bicarbonate, Squalane, Tocopheryl Acetate, Triethanolamine, Undecylenic Acid, Urea, Water, Xanthan Gum

Purpose…………………………………….. Antifungal